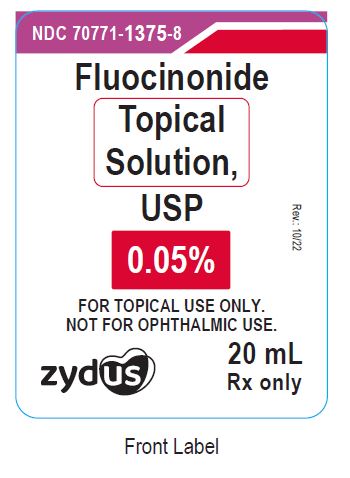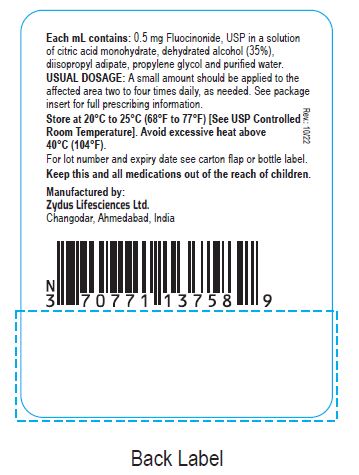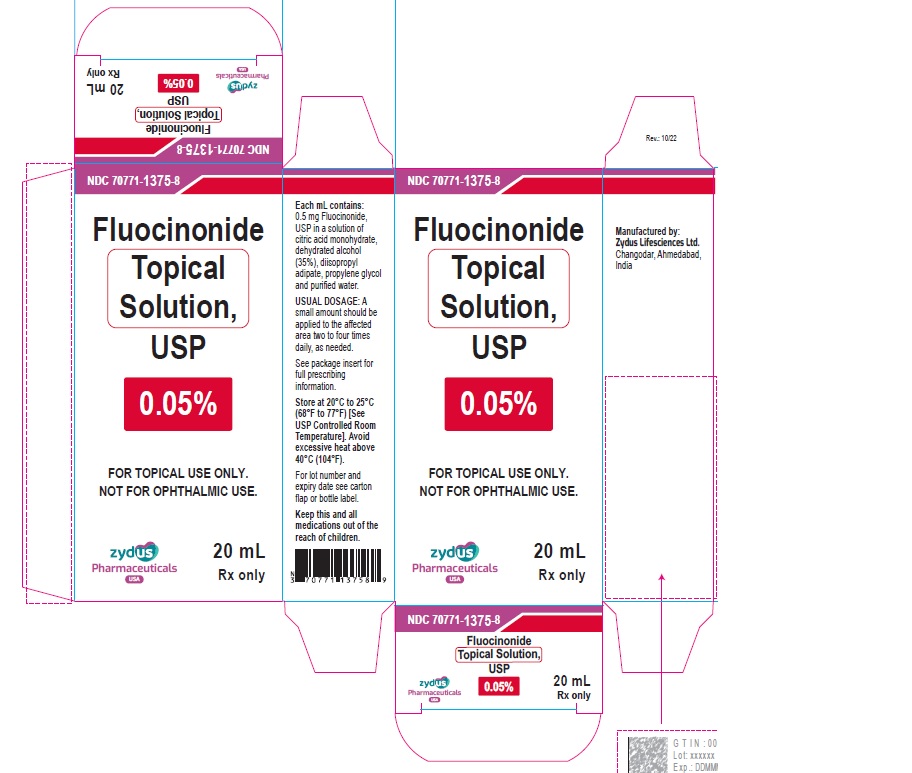 DRUG LABEL: Fluocinonide
NDC: 70771-1375 | Form: SOLUTION
Manufacturer: Zydus Lifesciences Limited
Category: prescription | Type: HUMAN PRESCRIPTION DRUG LABEL
Date: 20241130

ACTIVE INGREDIENTS: FLUOCINONIDE 0.5 mg/1 mL
INACTIVE INGREDIENTS: ALCOHOL; CITRIC ACID MONOHYDRATE; DIISOPROPYL ADIPATE; PROPYLENE GLYCOL; WATER

Fluocinonide topical solution USP, 0.05%

PACKAGE LABEL.PRINCIPAL DISPLAY PANEL

NDC 70771-1375-8

Fluocinonide topical solution USP, 0.05%

Rx only

20 mL